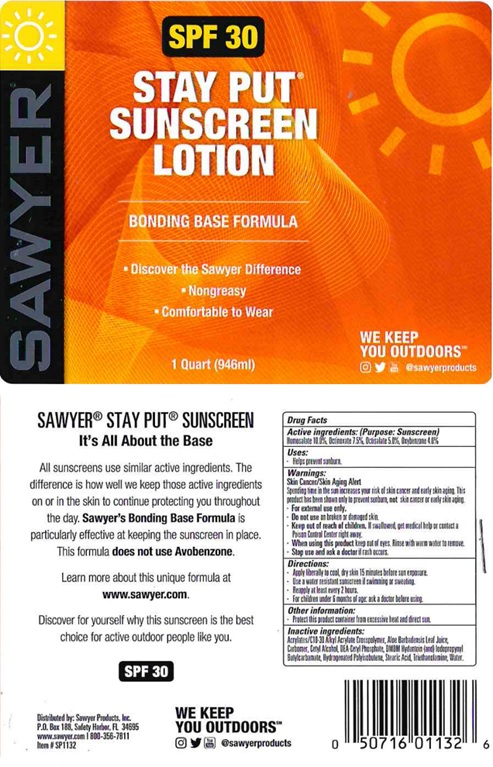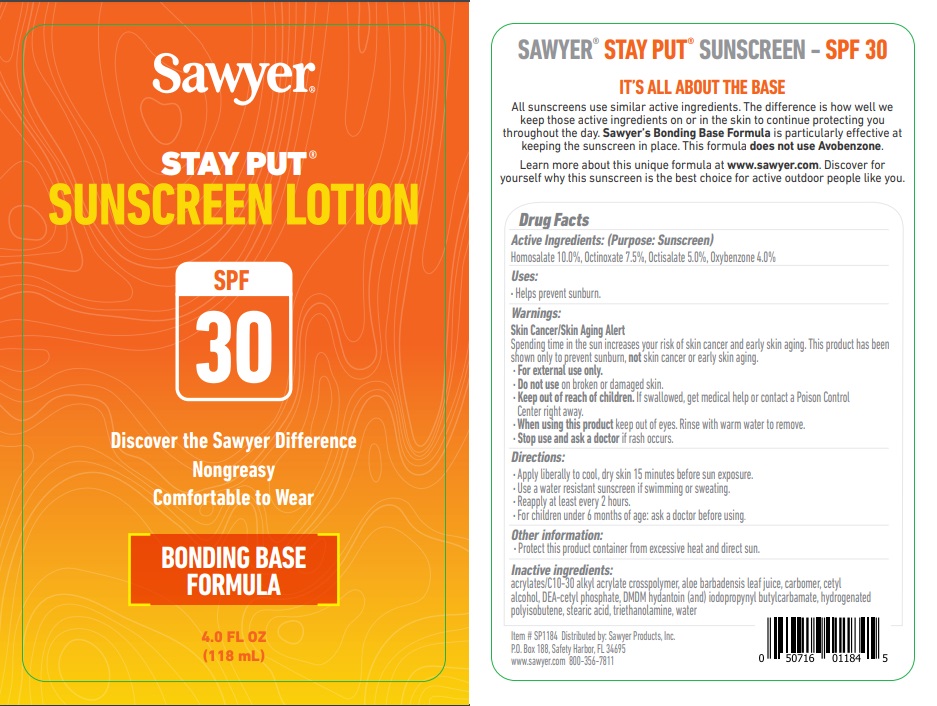 DRUG LABEL: Sawyer SPF 30
NDC: 73440-1184 | Form: LOTION
Manufacturer: Cross Brands Contract Filling
Category: otc | Type: HUMAN OTC DRUG LABEL
Date: 20210412

ACTIVE INGREDIENTS: OXYBENZONE 37.84 g/946 g; OCTISALATE 47.3 g/946 g; OCTINOXATE 70.95 g/946 g; HOMOSALATE 94.6 g/946 g
INACTIVE INGREDIENTS: WATER 506.49 g/946 g

Sawyer SPF 30 Sunscreen